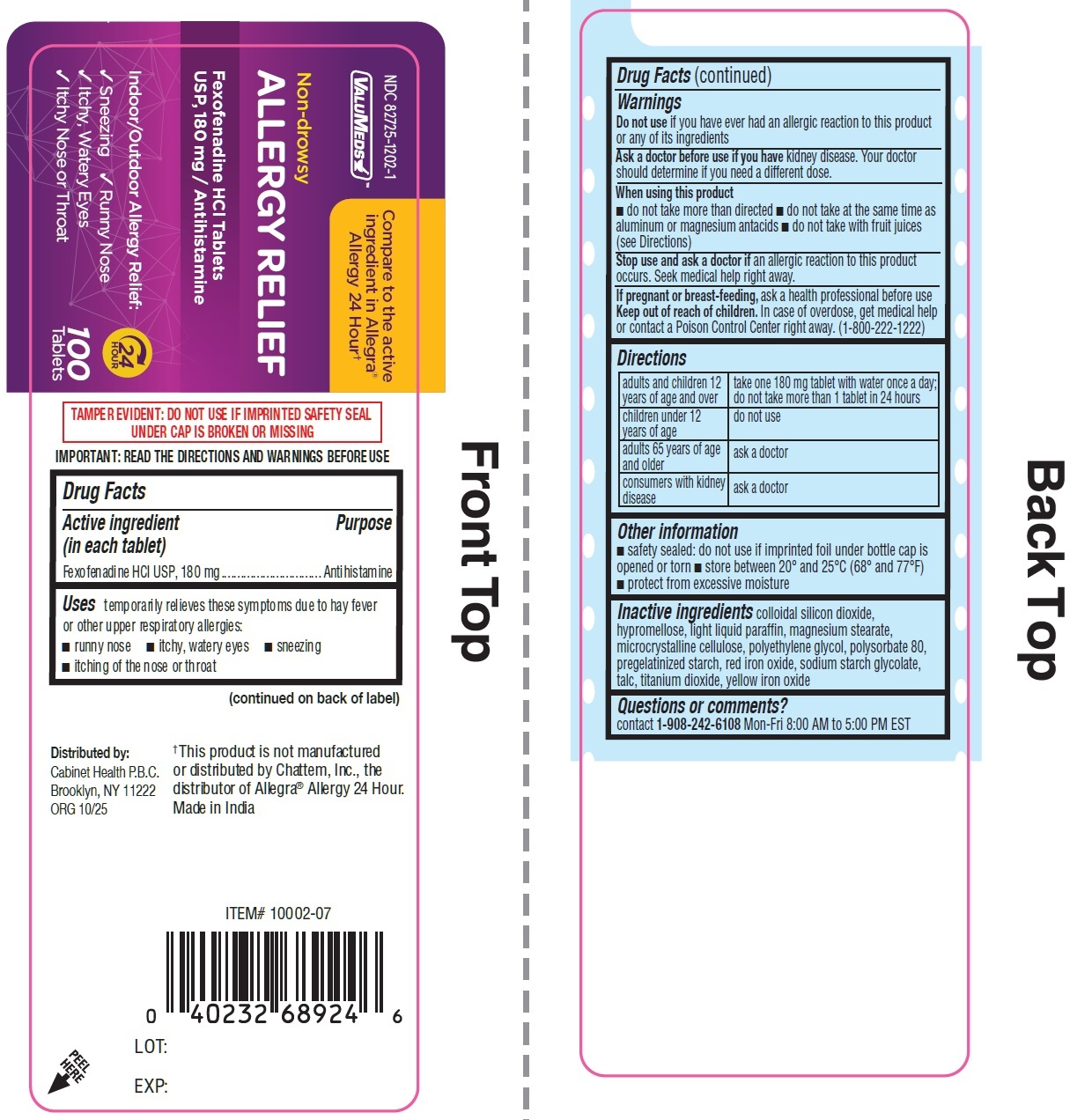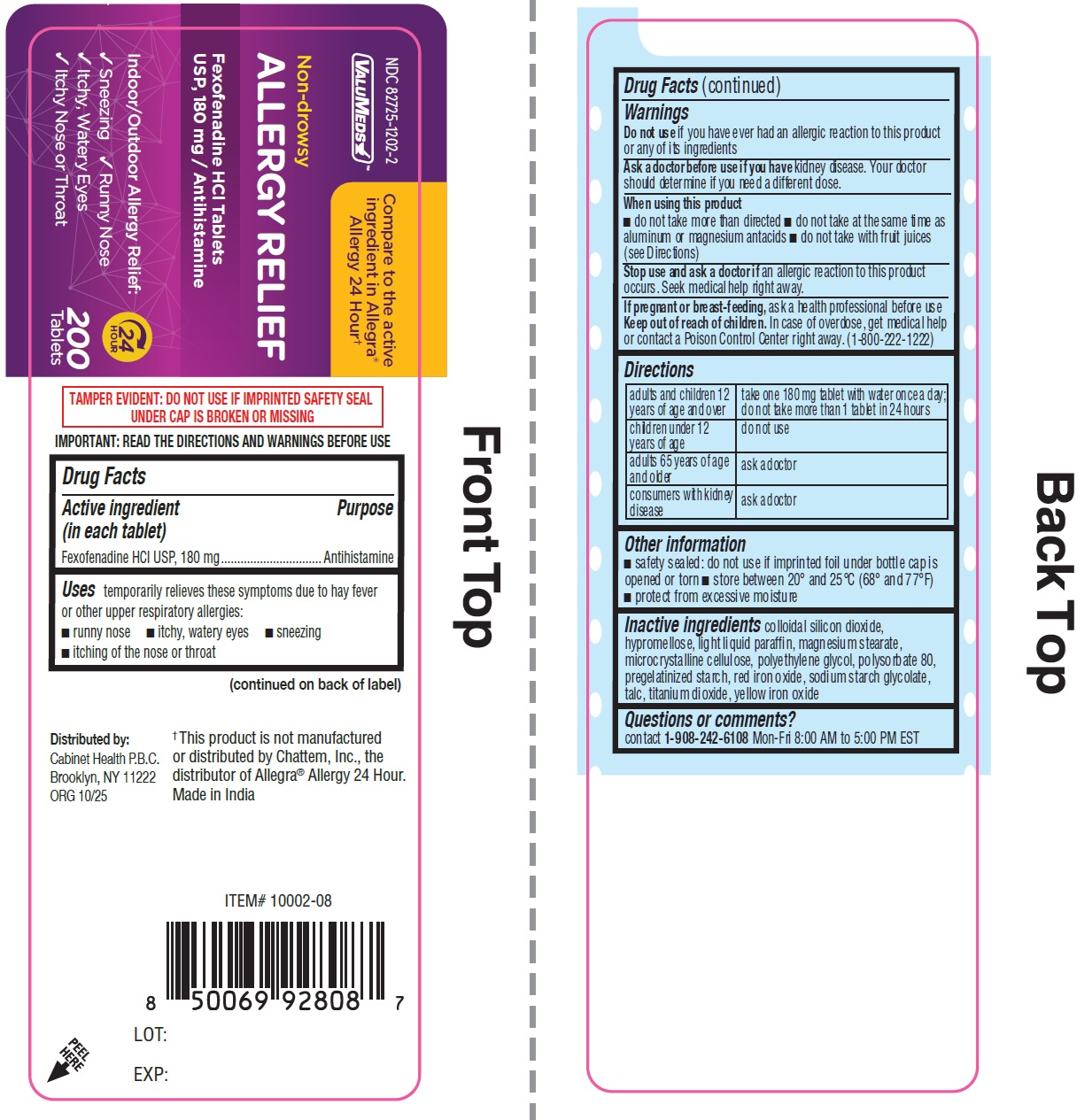 DRUG LABEL: ValuMeds Non-Drowsy Allergy Relief Fexofenadine HCl
NDC: 82725-1202 | Form: TABLET
Manufacturer: Cabinet Health P.B.C.
Category: otc | Type: HUMAN OTC DRUG LABEL
Date: 20260106

ACTIVE INGREDIENTS: FEXOFENADINE HYDROCHLORIDE 180 mg/1 1
INACTIVE INGREDIENTS: SILICON DIOXIDE; HYPROMELLOSE, UNSPECIFIED; LIGHT MINERAL OIL; MAGNESIUM STEARATE; MICROCRYSTALLINE CELLULOSE; POLYETHYLENE GLYCOL, UNSPECIFIED; POLYSORBATE 80; FERRIC OXIDE RED; SODIUM STARCH GLYCOLATE TYPE A; TALC; TITANIUM DIOXIDE; FERRIC OXIDE YELLOW

ValuMeds Non-Drowsy Allergy Relief, Fexofenadine HCl

Active ingredient

Fexofenadine HCl USP, 180 mg

Purpose

Antihistamine

Uses

temporarily relieves these symptoms due to hay fever or other upper respiratory allergies:
■ runny nose ■ itchy, watery eyes ■ sneezing ■ itching of the nose or throat

Warnings

Do not use

if you have ever had an allergic reaction to this product or any of its ingredients

Ask a doctor before use if you have

kidney disease. Your doctor should determine if you need a different dose.

When using this product

■ do not take more than directed ■ do not take at the same time as aluminum or magnesium antacids ■ do not take with fruit juices (see Directions)

Stop use and ask a doctor if

an allergic reaction to this product occurs. Seek medical help right away.

If pregnant or breast-feeding,

ask a health professional before use

Keep out of reach of children.

In case of overdose, get medical help or contact a Poison Control Center right away. (1-800-222-1222)

Directions

adults and children 12 years of age and over | take one 180 mg tablet with water once a day; do not take more than 1 tablet in 24 hours
children under 12 years of age | do not use
adults 65 years of age and older | ask a doctor
consumers with kidney disease | ask a doctor

Other information

■ safety sealed: do not use if imprinted foil under bottle cap is opened or torn ■ store between 20° and 25°C (68° and 77°F) ■ protect from excessive moisture

Inactive ingredients

colloidal silicon dioxide, hypromellose, light liquid paraffin, magnesium stearate, microcrystalline cellulose, polyethylene glycol, polysorbate 80, pregelatinized starch, red iron oxide, sodium starch glycolate, talc, titanium dioxide, yellow iron oxide

Questions or comments?

contact 1-908-242-6108Mon-Fri 8:00 AM to 5:00 PM EST